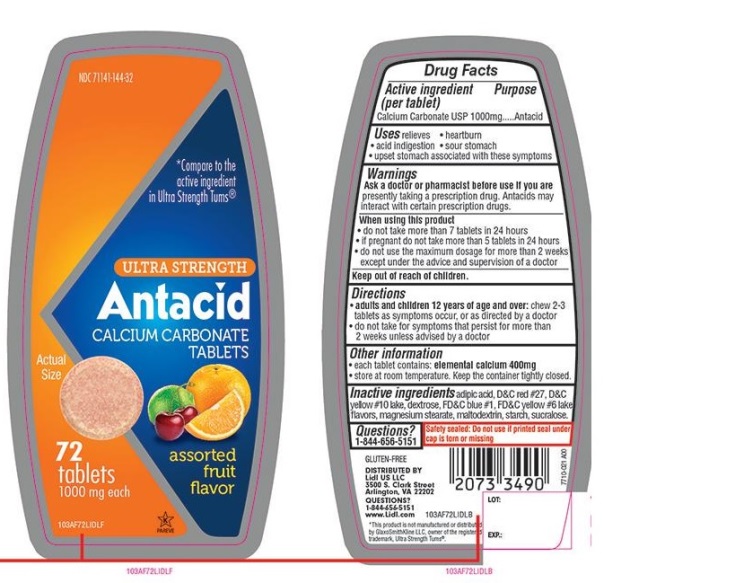 DRUG LABEL: Lidl Ultra Strength Antacid Calcium Carbonate

NDC: 71141-144 | Form: TABLET, CHEWABLE
Manufacturer: Lidl US LLC
Category: otc | Type: HUMAN OTC DRUG LABEL
Date: 20250919

ACTIVE INGREDIENTS: CALCIUM CARBONATE 1000 mg/1 1
INACTIVE INGREDIENTS: ADIPIC ACID; D&C RED NO. 27; D&C YELLOW NO. 10; DEXTROSE, UNSPECIFIED FORM; FD&C BLUE NO. 1; FD&C YELLOW NO. 6; MAGNESIUM STEARATE; MALTODEXTRIN; STARCH, CORN; SUCRALOSE

LIDL Ultra Strength Antacid Calcium Carbonate Chewable Tablets

Active ingredient (per tablet)

Calcium Carbonate USP 1000mg

Purpose

Antacid

Uses

relieves

- heartburn
- acid indigestion
- sour stomach
- upset stomach associated with these symptoms

Warnings

Ask a doctor or pharmacist before use if you arepresently taking a prescription drug. Antacids may interact with certain prescription drugs.

When using this product

- do not take more than 7 tablets in 24 hours
- if pregnant do not take more than 5 tablets in 24 hours
- do not use the maximum dosage for more than 2 weeks except under the advice and supervision of a doctor.

Directions

- adults and children 12 years of age and over:chew 2-3 tablets as symptoms occur, or as directed by a doctor
- do not take for symptoms that persist for more than 2 weeks unless advised by a doctor

Other information

- each tablet contains: elemental calcium 400mg
- Store at room temperature. Keep the container tightly closed.

Inactive ingredients

adipic acid, D&C red #27, D&C yellow #10 lake, dextrose, FD&C blue #1, FD&C yellow #6 lake, flavors, magnesium stearate, maltodextrin, starch, sucralose.

Questions?

1-844-656-5151

Safety sealed: Do not use if printed seal under cap is torn or missing

Package/Label Principal Display Panel

NDC 71141-144-32

*Compare to the active ingredient in Ultra Strength Tums®

ULTRA STRENGTH

Antacid

CALCIUM CARBONATE TABLETS

assorted fruit flavors

72 tablets

1000 mg each

K

PAREVE

GLUTEN- FREE

DISTRIBUTED BY

Lidl US LLC

3500 S. Clark Street

Arlington, VA 22202

QUESTIONS?

1-844-656-5151

www.Lidl.com

*This product is not manufactured or distributed by GlaxoSmithKline LLC, owner of the registered trademark, Ultra StrengthTums®.